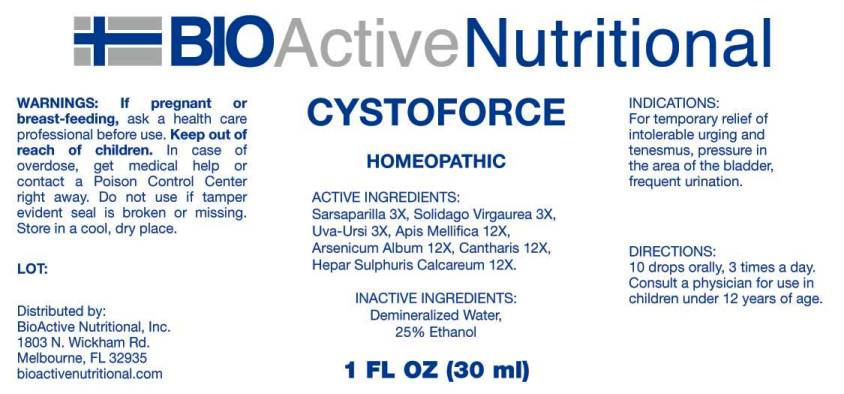 DRUG LABEL: Cystoforce
NDC: 43857-0170 | Form: LIQUID
Manufacturer: BioActive Nutritional, Inc.
Category: homeopathic | Type: HUMAN OTC DRUG LABEL
Date: 20231211

ACTIVE INGREDIENTS: SMILAX ORNATA ROOT 3 [hp_X]/1 mL; SOLIDAGO VIRGAUREA FLOWERING TOP 3 [hp_X]/1 mL; ARCTOSTAPHYLOS UVA-URSI LEAF 3 [hp_X]/1 mL; APIS MELLIFERA 12 [hp_X]/1 mL; ARSENIC TRIOXIDE 12 [hp_X]/1 mL; LYTTA VESICATORIA 12 [hp_X]/1 mL; CALCIUM SULFIDE 12 [hp_X]/1 mL
INACTIVE INGREDIENTS: ALCOHOL; WATER

DRUG FACTS:

ACTIVE INGREDIENTS:

Sarsaparilla 3X, Solidago Virgaurea 3X, Uva Ursi 3X, Apis Mellifica 12X, Arsenicum Album 12X, Cantharis 12X, Hepar Sulphuris Calcareum 12X.

INDICATIONS:

For temporary relief of intolerable urging and tenesmus, pressure in the area in the bladder, frequent urination.

WARNINGS:

If pregnant or breast-feeding, ask a health care professional before use.

Keep out of reach of children. In case of overdose, get medical help or contact a Poison Control Center right away.

Do not use if tamper evident seal is broken or missing.

Store in cool, dry place.

DIRECTIONS:

10 drops orally, 3 times a day. Consult a physician for use in children under 12 years of age.

INACTIVE INGREDIENTS:

Demineralized Water, 25% Ethanol.

Keep out of reach of children. In case of overdose, get medical help or contact a Poison Control Center right away.

INDICATIONS:

For temporary relief of intolerable urging and tenesmus, pressure in the area in the bladder, frequent urination.

QUESTIONS:

Distributed by:
BioActive Nutritional, Inc.
1803 N. Wickham Rd.
Melbourne, FL 32935
bioactivenutritional.com

PACKAGE LABEL DISPLAY:

BIOActive Nutritional

CYSTOFORCE

HOMEOPATHIC

1 FL OZ (30 ml)